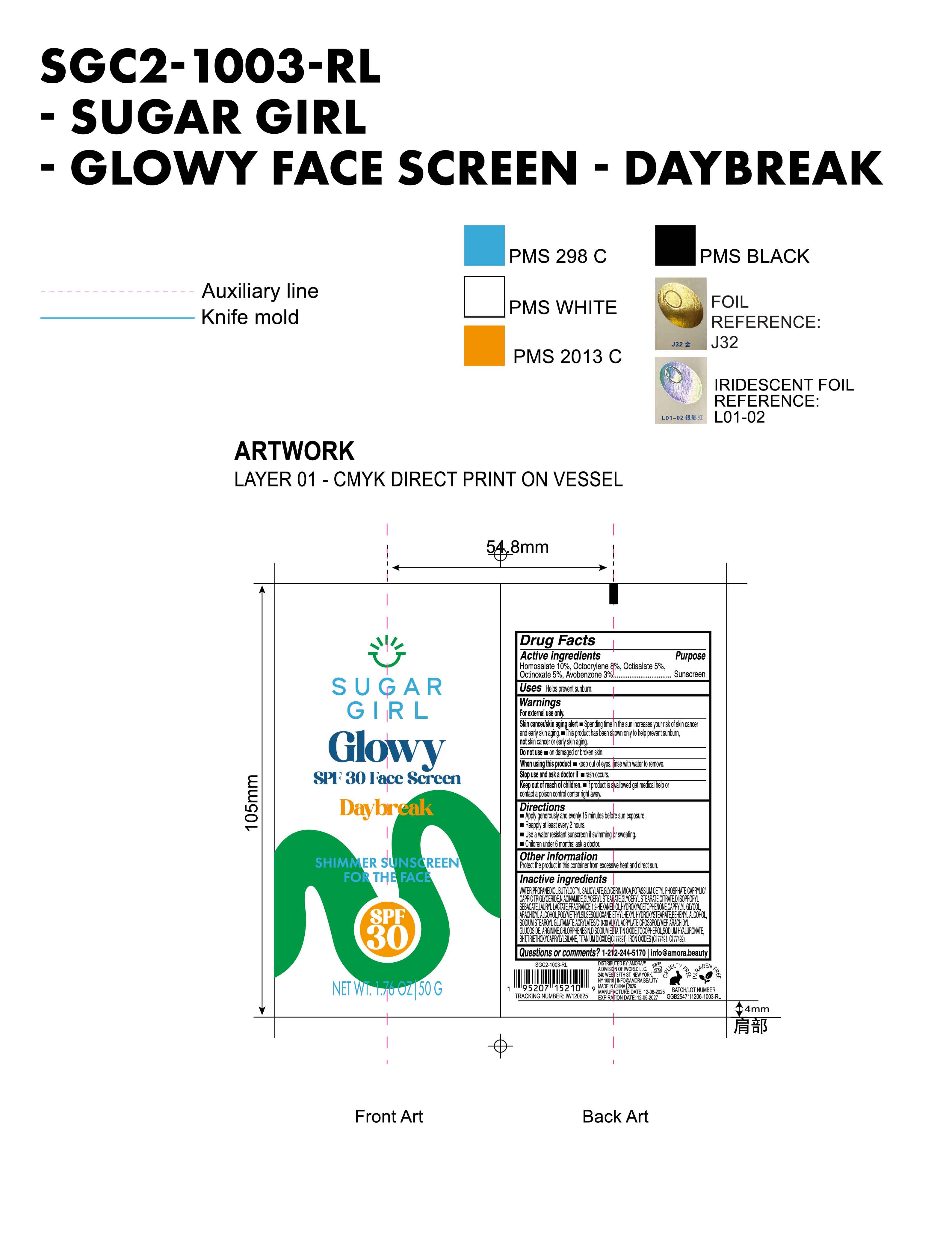 DRUG LABEL: Sugargirl Glowy SPF 30 Face Screen  daybreak Shimmer Sunscreen for the face
NDC: 85161-137 | Form: CREAM
Manufacturer: Longway Technology(Guangzhou)Co.,Ltd.
Category: otc | Type: HUMAN OTC DRUG LABEL
Date: 20251221

ACTIVE INGREDIENTS: HOMOSALATE 0.1 g/1 g; AVOBENZONE 0.03 g/1 g; OCTINOXATE 0.05 g/1 g; OCTISALATE 0.05 g/1 g; OCTOCRYLENE 0.08 g/1 g
INACTIVE INGREDIENTS: ETHYLHEXYL HYDROXYSTEARATE; TOCOPHEROL; TRIETHOXYCAPRYLYLSILANE; CAPRYLYL GLYCOL; ACRYLATES/C10-30 ALKYL ACRYLATE CROSSPOLYMER (60000 MPA.S); FRAGRANCE 13576; DIISOPROPYL SEBACATE; CHLORPHENESIN; POTASSIUM CETYL PHOSPHATE; ARACHIDYL ALCOHOL; GLYCERYL STEARATE CITRATE; EDETATE DISODIUM; WATER; MICA; GLYCERYL STEARATE; GLYCERIN; ARACHIDYL GLUCOSIDE; PROPANEDIOL; BUTYLOCTYL SALICYLATE; 1,2-HEXANEDIOL; HYDROXYACETOPHENONE; BEHENYL ALCOHOL; SODIUM STEAROYL GLUTAMATE; ARGININE; CI 77491; TIN OXIDE; POLYMETHYLSILSESQUIOXANE (11 MICRONS); CI 77492; SODIUM HYALURONATE; BHT; CI 77891; CAPRYLIC/CAPRIC TRIGLYCERIDE; NIACINAMIDE; LAURYL LACTATE

ACTIVE INGREDIENT

Homosalate 10%, Octocrylene 8%, Octisalate 5%, Octinoxate 5%, Avobenzone 3%

INACTIVE INGREDIENT

WATER, PROPANEDIOL, BUTYLOCTYL SALICYLATE, GLYCERIN, MICA, POTASSIUM CETYL PHOSPHATE, CAPRYLIC/CAPRIC TRIGLYCERIDE, NIACINAMIDE, GLYCERYL STEARATE, GLYCERYL STEARATE CITRATE, DIISOPROPYL SEBACATE, LAURYL LACTATE, FRAGRANCE, 1,2-HEXANEDIOL, HYDROXYACETOPHENONE, CAPRYLYL GLYCOL, ARACHIDYL ALCOHOL, POLYMETHYLSILSESQUIOXANE, ETHYLHEXYL HYDROXYSTEARATE, BEHENYL ALCOHOL, SODIUM STEAROYL GLUTAMATE, ACRYLATES/C10-30 ALKYL ACRYLATE CROSSPOLYMER, ARACHIDYL GLUCOSIDE, ARGININE, CHLORPHENESIN, DISODIUM EDTA, TIN OXIDE, TOCOPHEROL, SODIUM HYALURONATE, BHT, TRIETHOXYCAPRYLYLSILANE, TITANIUM DIOXIDE(CI 77891), IRON OXIDES（CI 77491,CI 77492）

Keep out of reach of children.

If product is swallowed get medical help or contact a poison control center right away.

PURPOSE

Sunscreen

QUESTIONS

1-212-244-5170info@amora.beauty

OTHER SAFETY INFORMATION

Protect the product in this container from excessive heat and direct sun.

DOSAGE AND ADMINISTRATION

Apply generously and evenly 15 minutes before sun exposure.

Reapply at least every 2 hours.

Use a water resistant sunscreen if swimming or sweating.

Children under 6 months: ask a doctor.

INDICATIONS AND USAGE

Helps prevent sunburn.

Warnings
For external use only
Skin cancer/skin aging alert
Spending time in the sun increases your risk of skin cancer and early skin aging.
This product has been shown only to help prevent sunburn,not skin cancer or early skin aging.

Do not use on damaged or broken skin.

When using this product keep out of eyes.rinse with water to remove.

Stop use and ask a doctor if rash occurs.

Keep out of reach of children. If product is swallowed get medical help or contact a poison control center right away.